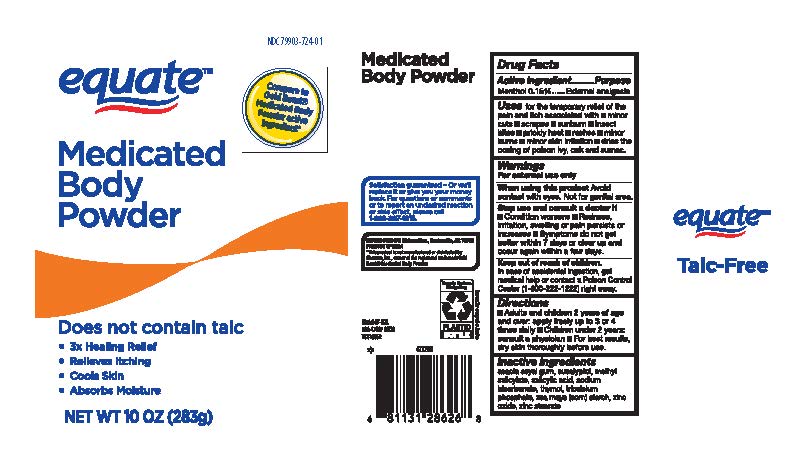 DRUG LABEL: Medicated Body

NDC: 79903-724 | Form: POWDER
Manufacturer: Walmart Stores Inc
Category: otc | Type: HUMAN OTC DRUG LABEL
Date: 20260212

ACTIVE INGREDIENTS: MENTHOL 0.42 g/283 g
INACTIVE INGREDIENTS: SODIUM BICARBONATE; TRICALCIUM PHOSPHATE; ACACIA; EUCALYPTUS OIL; MENTHYL SALICYLATE, (+/-)-; SALICYLIC ACID; THYMOL; ZINC STEARATE; ZINC OXIDE; ZEA MAYS WHOLE

Equated Medicated Body Powder - 202

Drug Facts Active Ingredients

Menthol 0.15 %

Purpose

External Analgesic

Uses

for the temporary relief of the pain and itch associated with

- minor cuts
- scrapes
- sunburn
- insect bites
- prickly heat
- rashes
- minor burns
- minor skin irritations
- dries the oozing of poison ivy, oak and sumac.

Warnings

For external use only

When usin this product

Avoid contact with eyes. Not for genital area.

Stop use and ask a doctor if

- condition worsens
- Redness, irritation, swelling or pain persist or increases
- symptoms do not get better within 7 days or clear up and occur again within a few days

Keep out of reach of children. In case of accidental ingestion, get medical help or contact a Poison Control Center (1-800-222-1222) right away.

Directions

- adults and children 2 years of age and over, apply freely up to 3 or 4 times daily
- Children under 2 years: consult a physician
- for best results, dry skin thoroughly before use

Inactive Ingredients

acacia seyl gum, eucalyptol, methyl salicylate, salicylic acid, sodium bicarbonate, thymol, tricalciun phosphate, zea mays (corn stach), zinc oxide, zinc stearate